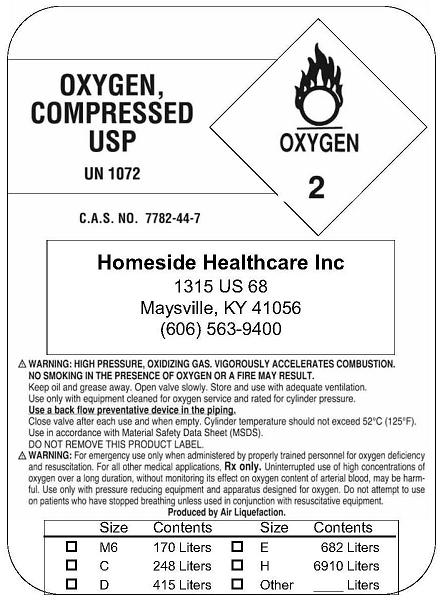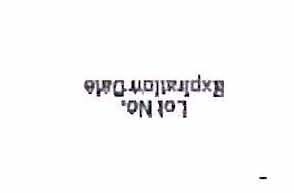 DRUG LABEL: Oxygen
NDC: 24319-0001 | Form: GAS
Manufacturer: Homeside Healthcare, Inc. 
Category: prescription | Type: HUMAN PRESCRIPTION DRUG LABEL
Date: 20091217

ACTIVE INGREDIENTS: Oxygen 99 L/100 L

Oxygen